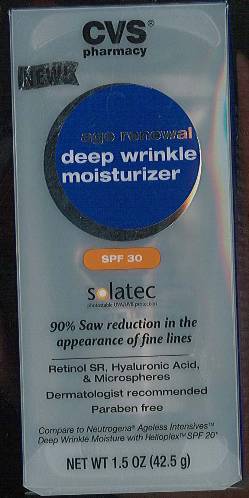 DRUG LABEL: age renewal deep wrinkle moisturizer
NDC: 68634-0029 | Form: CREAM
Manufacturer: AMCOL Health and Beauty Solutions, Inc.
Category: otc | Type: HUMAN OTC DRUG LABEL
Date: 20100209

ACTIVE INGREDIENTS: Homosalate 0.1 g/1 g; Octisalate 0.05 g/1 g; Oxybenzone 0.02 g/1 g; Avobenzone 0.02 g/1 g; Octocrylene 0.015 g/1 g

age renewal deep wrinkle moisturizer

ACTIVE INGREDIENT

Active Ingredients: Homosalate 10%, Octisalate 5%, Oxybenzone 2%, Avobenzone 2%, Octocrylene 1.5%